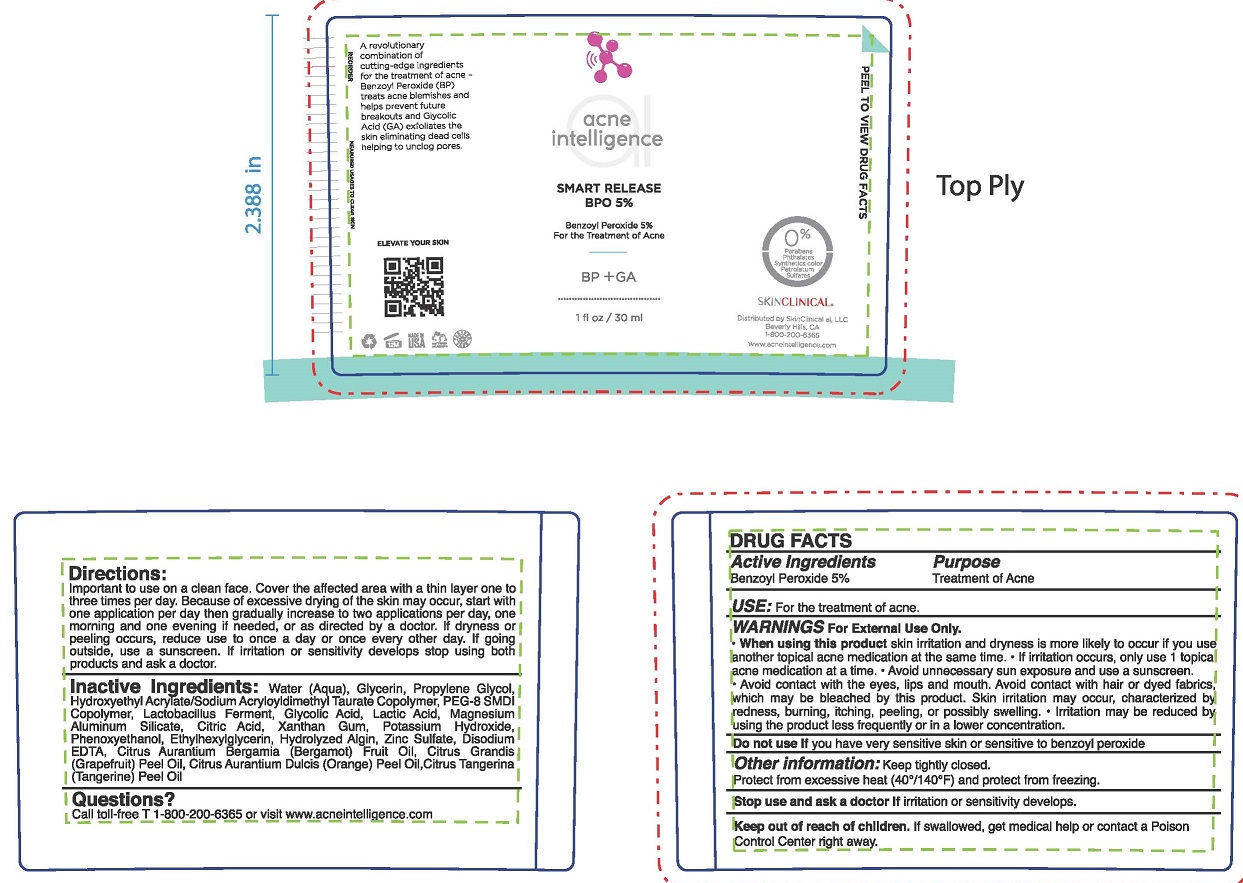 DRUG LABEL: SMART RELEASE BPO
NDC: 73110-102 | Form: LOTION
Manufacturer: SkinClinical AI, LLC
Category: otc | Type: HUMAN OTC DRUG LABEL
Date: 20190629

ACTIVE INGREDIENTS: BENZOYL PEROXIDE 5 g/100 mL
INACTIVE INGREDIENTS: WATER; GLYCERIN; PROPYLENE GLYCOL; HYDROXYETHYL ACRYLATE/SODIUM ACRYLOYLDIMETHYL TAURATE COPOLYMER (100000 MPA.S AT 1.5%); PEG-8/SMDI COPOLYMER; LACTOBACILLUS REUTERI; GLYCOLIC ACID; LACTIC ACID; MAGNESIUM ALUMINUM SILICATE; ANHYDROUS CITRIC ACID; XANTHAN GUM; POTASSIUM HYDROXIDE; PHENOXYETHANOL; ETHYLHEXYLGLYCERIN; SODIUM ALGINATE; ZINC SULFATE; EDETATE DISODIUM; BERGAMOT OIL; GRAPEFRUIT OIL; ORANGE OIL; TANGERINE PEEL

SMART RELEASE BPO 5%

PURPOSE

TREATMENT OF ACNE

ACTIVE INGREDIENT

BENZOYL PEROXIDE 5%

USE

FOR THE TREATMENT OF ACNE

WARNINGS

FOR EXTERNAL USE ONLY.

- WHEN USING THIS PRODUCT SKIN IRRITATION AND DRYNESS IS MORE LIKELY TO OCCUR IF YOU USE ANOTHER TOPICAL ACNE MEDICATION AT THE SAME TIME.
- IF IRRITATION OCCURS, ONLY USE 1 TOPICAL ACNE MEDICATION AT A TIME.
- AVOID UNNECESSARY SUN EXPOSURE AND USE A SUNSCREEN. AVOID CONTACT WITH THE EYES, LIPS AND MOUTH. SKIN IRRITATION MAY OCCUR, CHARACTERIZED BY REDNESS, BURNING, ITCHINH, PEELING, OR POSSIBLY SWELLING.
- IRRITATION MAY BE REDUCED BY USING THE PRODUCT LESS FREQUENTLY OR IN A LOWER CONCENTRATION.

DO NOT USE IF YOU HAVE VERY SENSITIVE SKIN OR SENSITIVE TO BENZOYL PEROXIDE.

Stop use and ask a doctor if irritation or sensitivity develops.

OTHER INFORMATION

Keep tightly closed.
Protect from excessive heat (40°/140° F) and protect from freezing.

Keep out of reach of children. If swallowed, get medical help or contact a Poison Control Center right away..

DIRECTIONS

IMPORTANT TO USE ON A CLEAN FACE. COVER THE AFFECTED AREA WITH A THIN LAYER ONE TO THREE TIMES PER DAY. BECAUSE OF EXCESSIVE DRYING OF THE SKIN MAY OCCUR, START WITH ONE APPLICATION PER DAY THEN GRADUALLY INCREASE TO TWO APPLICATIONS PER DAY, ONE MORNING AND ONE EVENING IF NEEDED, OR AS DIRECTED BY A DOCTOR. IF DRYNESS OR PEELING OCCURS, REDUCE USE TO ONCE A DAY OR ONCE EVERY OTHER DAY. IF GOING OUTSIDE, USE A SUNSCREEN. IF IRRITATION OR SENSITIVITY DEVELOPS STOP USING BOTH PRODUCTS AND ASK A DOCTOR.

INACTIVE INGREDIENTS

Water (Aqua), Glycerin, Propylene Glycol, Hydroxyethyl Acrylate/Sodium Acryloyldimethyl Taurate Copolymer, PEG-8 SMDI Copolymer, Lactobacillus Ferment, Glycolic Acid, Lactic Acid, Magnesium Aluminum Silicate, Citric Acid, Xanthan Gum, Potassium Hydroxide, Phenoxyethanol, Ethylhexylglycerin, Hydrolyzed Algin, Zinc Sulfate, Disodium EDTA, Citrus Aurantium Bergamia (Bergamot) Fruit Oil, Citrus Grandis (Grapefruit) Peel Oil, Citrus Aurantium Dulcis (Orange) Peel Oil.Citrus Tangerina (Tangerine) Peel Oil

QUESTIONS?

Call toll-free T 1-800-200-6365 or visit www.acneintellifillnce.com